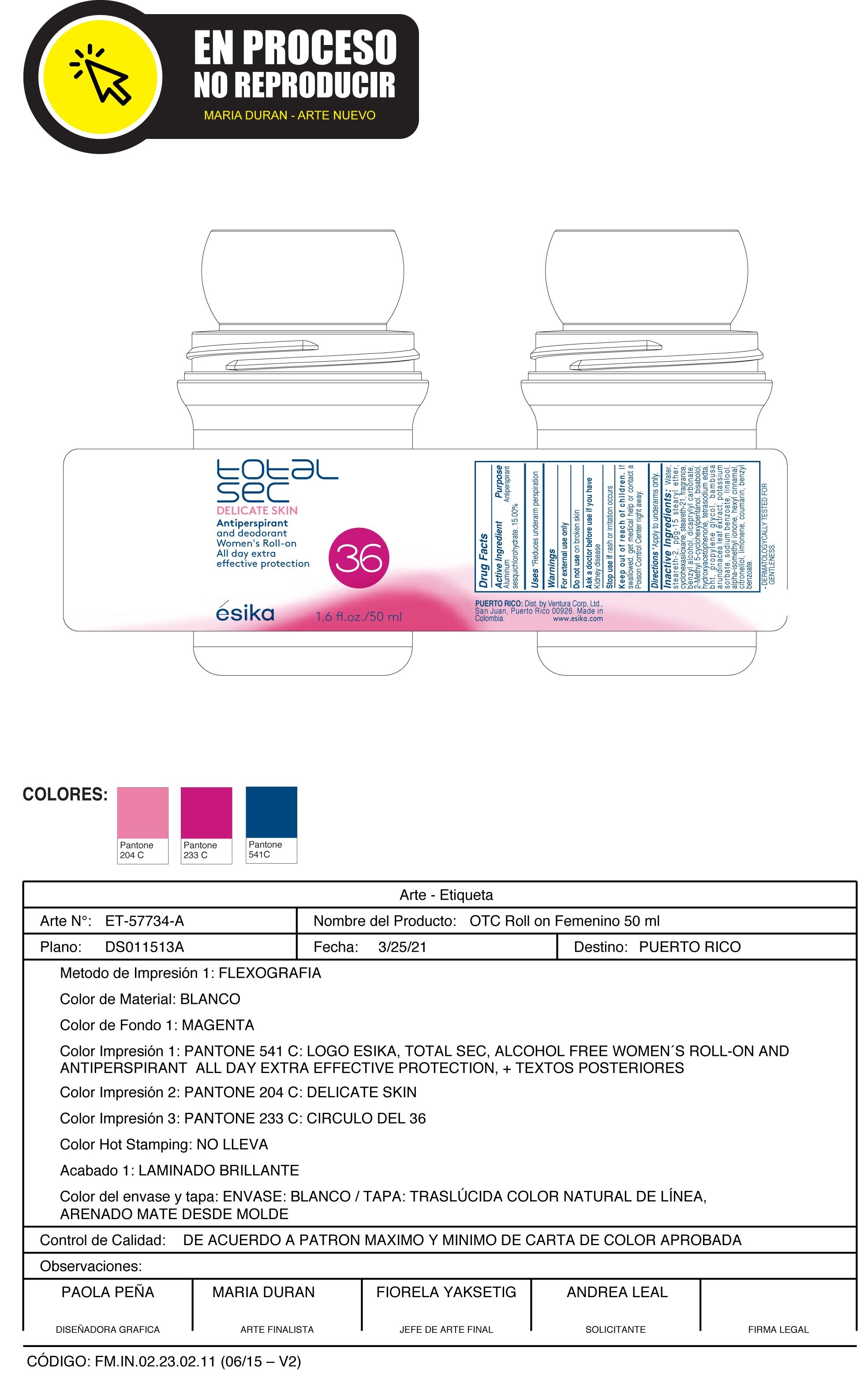 DRUG LABEL: esika total sec DELICATE SKIN Antiperspirant and deodorant Womens roll-on All day extra effective protection
NDC: 14141-961 | Form: EMULSION
Manufacturer: BEL STAR S A
Category: otc | Type: HUMAN OTC DRUG LABEL
Date: 20241028

ACTIVE INGREDIENTS: ALUMINUM SESQUICHLOROHYDRATE 15 g/100 mL
INACTIVE INGREDIENTS: DICAPRYLYL CARBONATE; 2-METHYL 5-CYCLOHEXYLPENTANOL; PROPYLENE GLYCOL; ISOMETHYL-.ALPHA.-IONONE; LEVOMENOL; BUTYLATED HYDROXYTOLUENE; BENZYL ALCOHOL; .ALPHA.-HEXYLCINNAMALDEHYDE; COUMARIN; LINALOOL, (+/-)-; BENZYL BENZOATE; EDETATE SODIUM; HYDROXYACETOPHENONE; STEARETH-2; CYCLOMETHICONE 6; STEARETH-21; LIMONENE, (+)-; WATER; PPG-15 STEARYL ETHER; BAMBUSA ARUNDINACEA LEAF; POTASSIUM SORBATE; SODIUM BENZOATE; .BETA.-CITRONELLOL, (R)-

esika total sec DELICATE SKIN Antiperspirant and deodorant Women's roll-on All day extra effective protection

Active Ingredient Purpose
Aluminum sesquichlorohydrate 15.00% Antiperspirant

Uses
Reduces underarm perspiration

Keep out of reach of children.If swallowed, get medical help or contact a Poison Control Center right away.

Stop use ifrash or irritation occurs

Warnings

For external use only

Do not useon broken skin

Ask a doctor before use if you havekidney disease

Directions
Apply to underarms only.

INACTIVE INGREDIENT

Inactive ingredients:Water, steareth-2, ppg-15 stearyl ether, cyclohexasiloxane, steareth-21, fragrance, benzyl alcohol, dicaprylyl carbonate, 2-methyl 5-cyclohexylpentanol, bisabolol, hydroxyacetophenone, tetrasodium edta, bht, propylene glycol, bambusa arundinacea leaf extract, potassium sorbate, sodium benzoate, linalool, alpha-isomethyl ionone, hexyl cinnamal, citronellol, limonene, coumarin, benzyl benzoate.

PACKAGE LABEL

total sec

DELICATE SKIN

Antiperspirant and deodorant

Women's Roll-on

All day extra effective protection

esika

1.6 fl. oz./ 50 ml